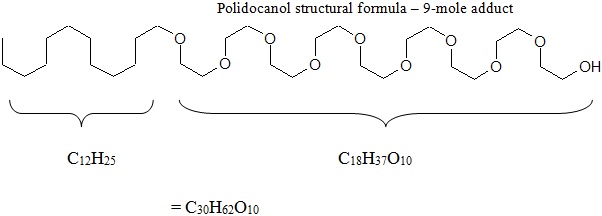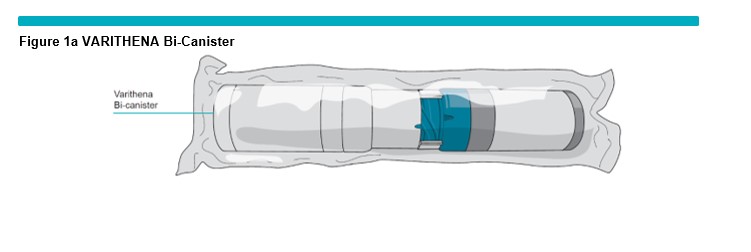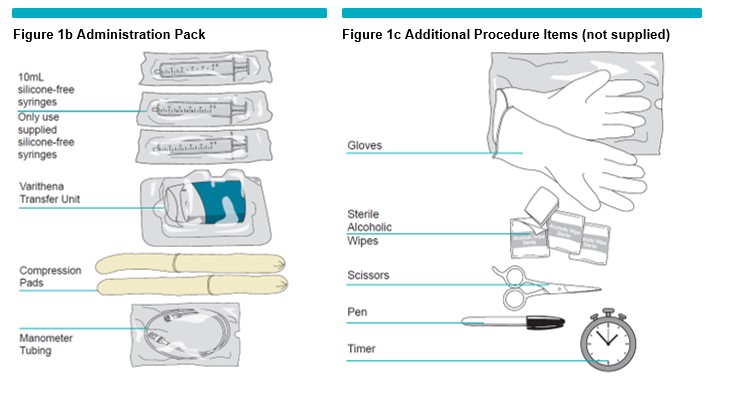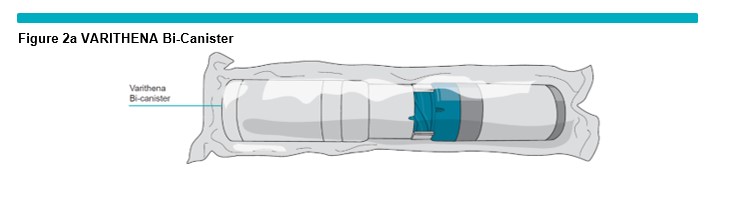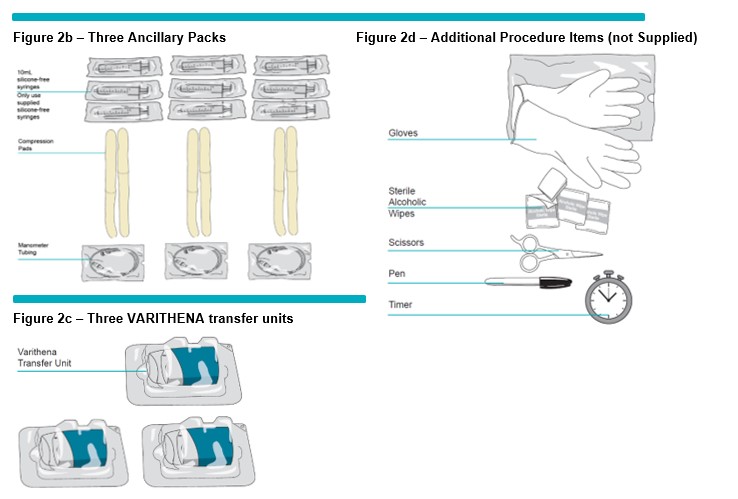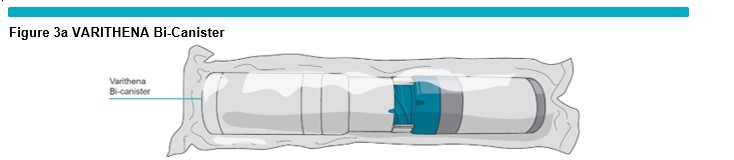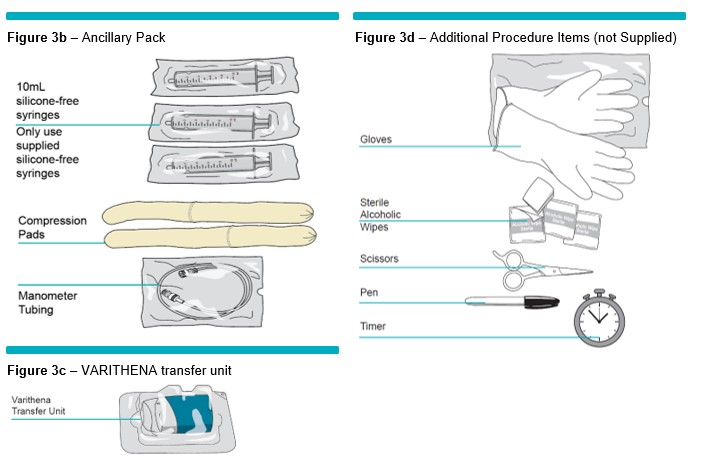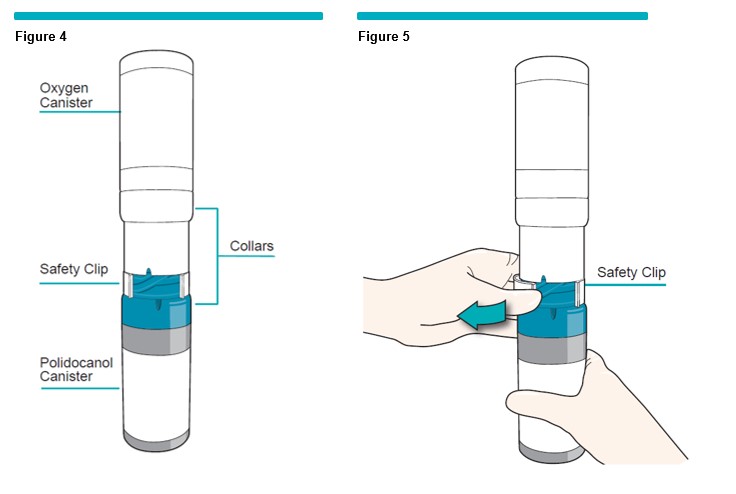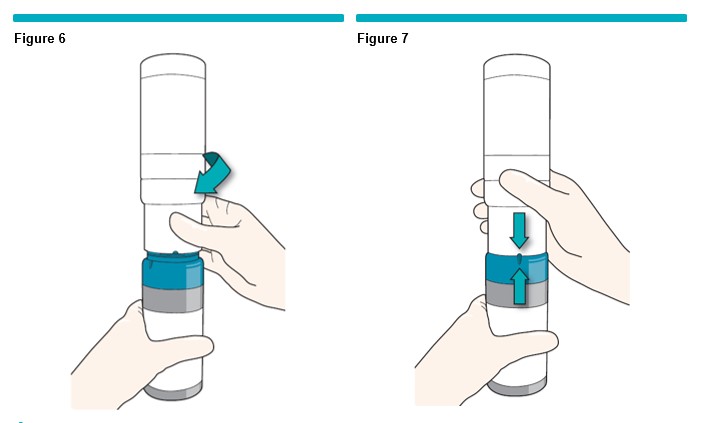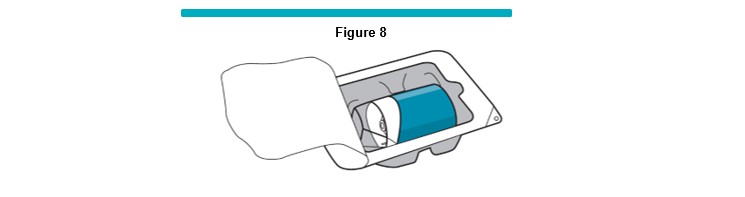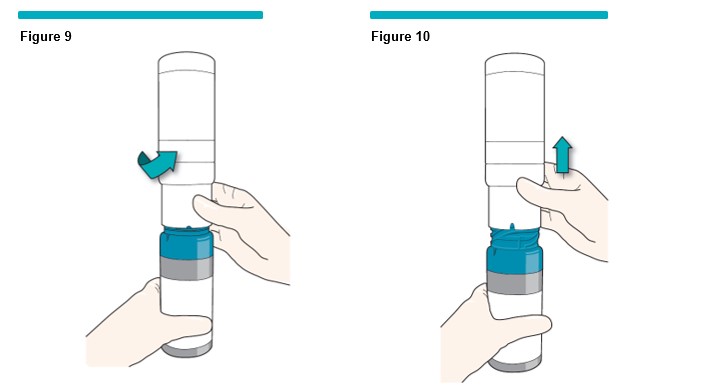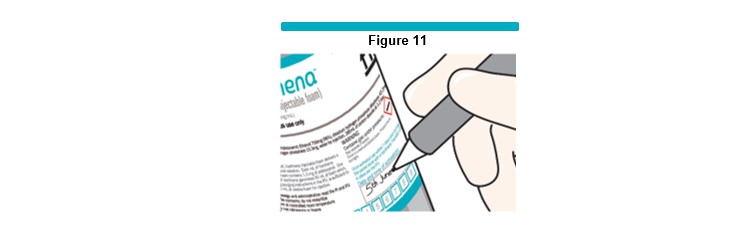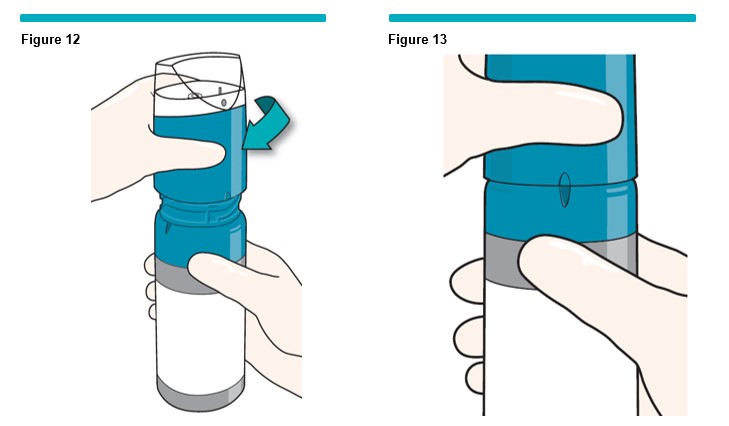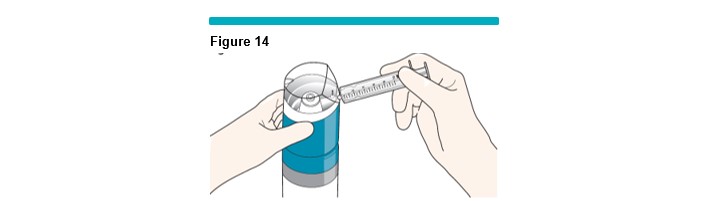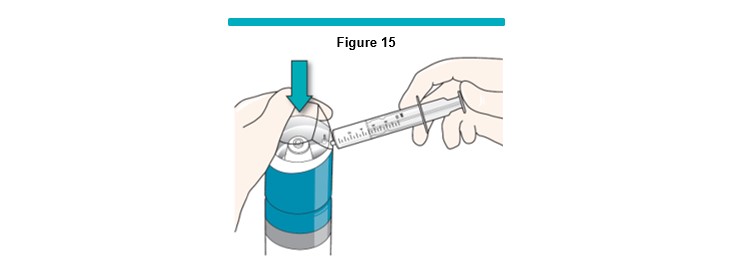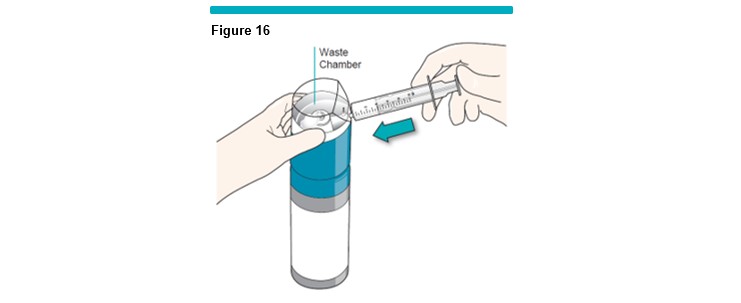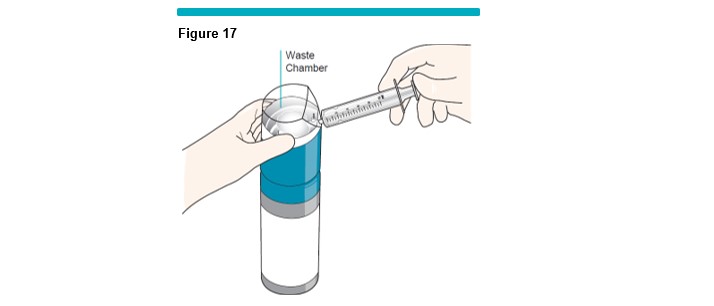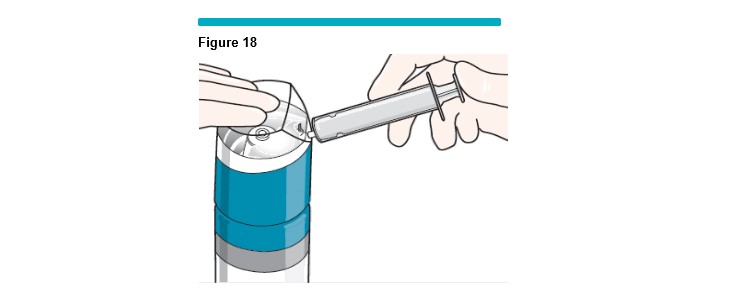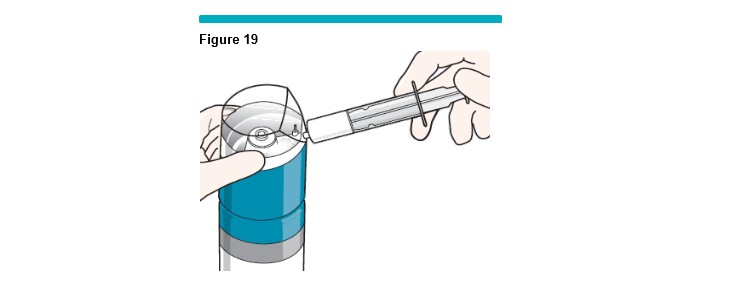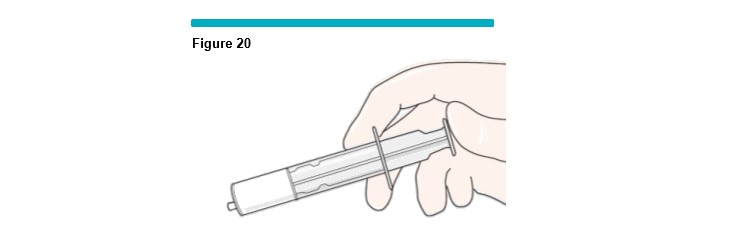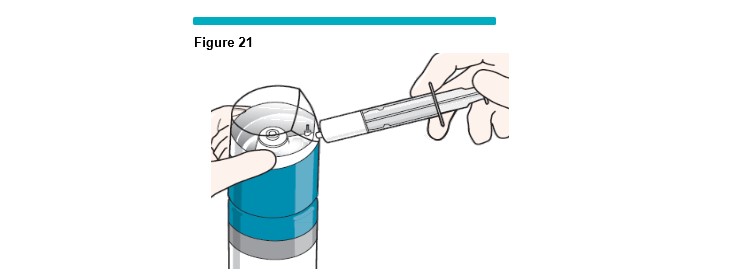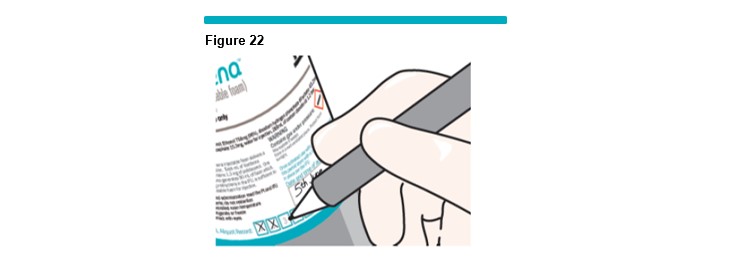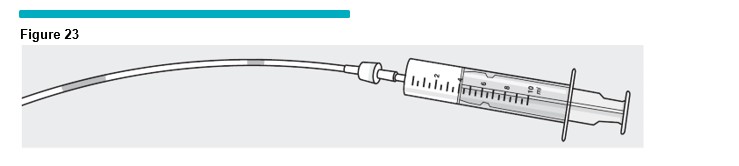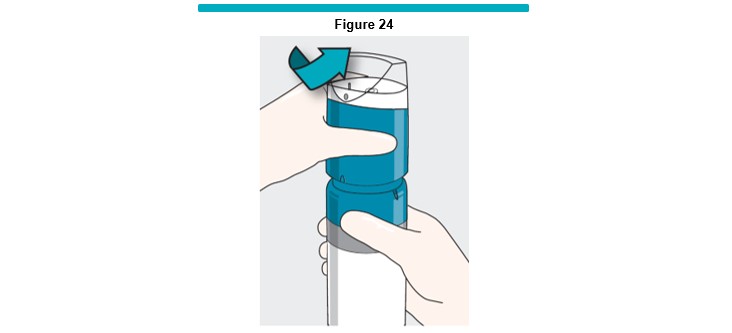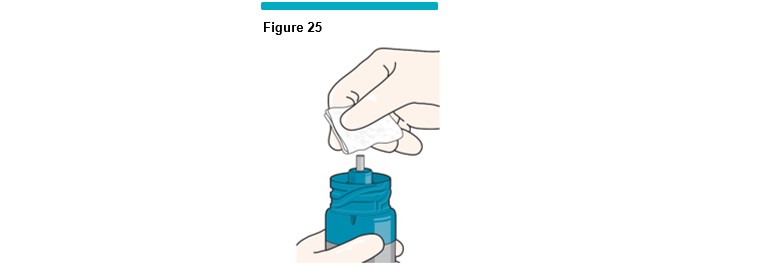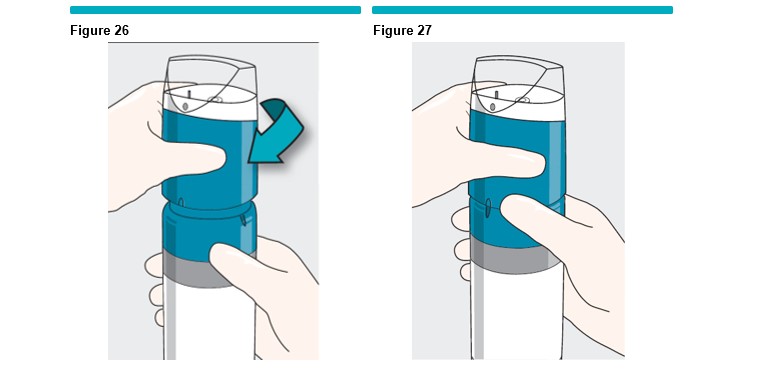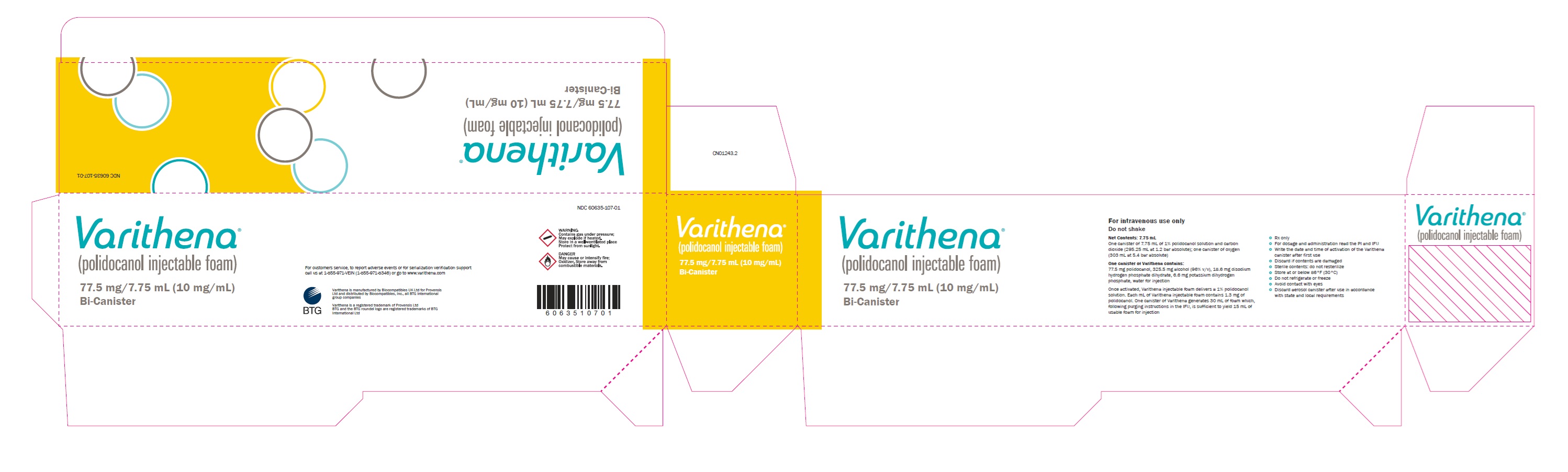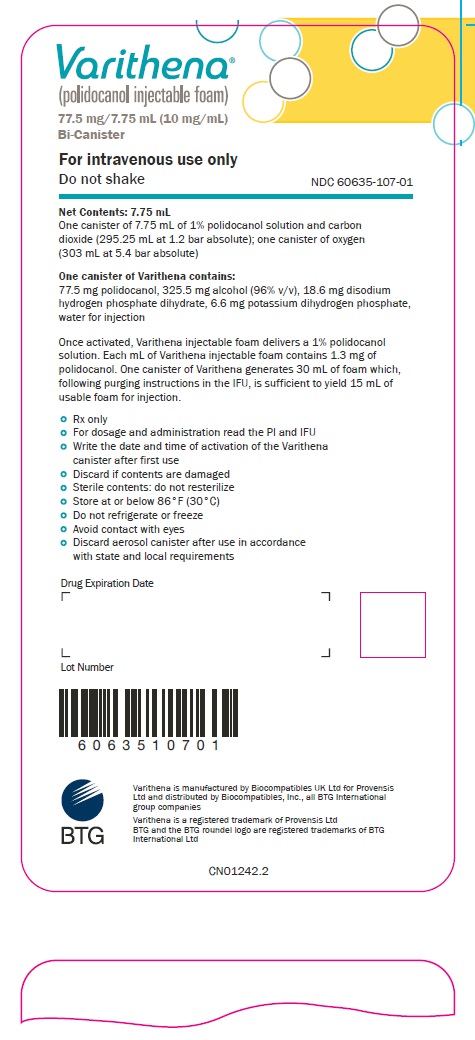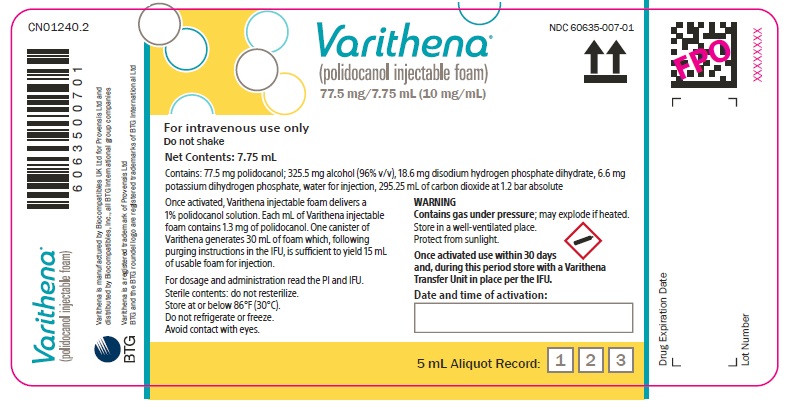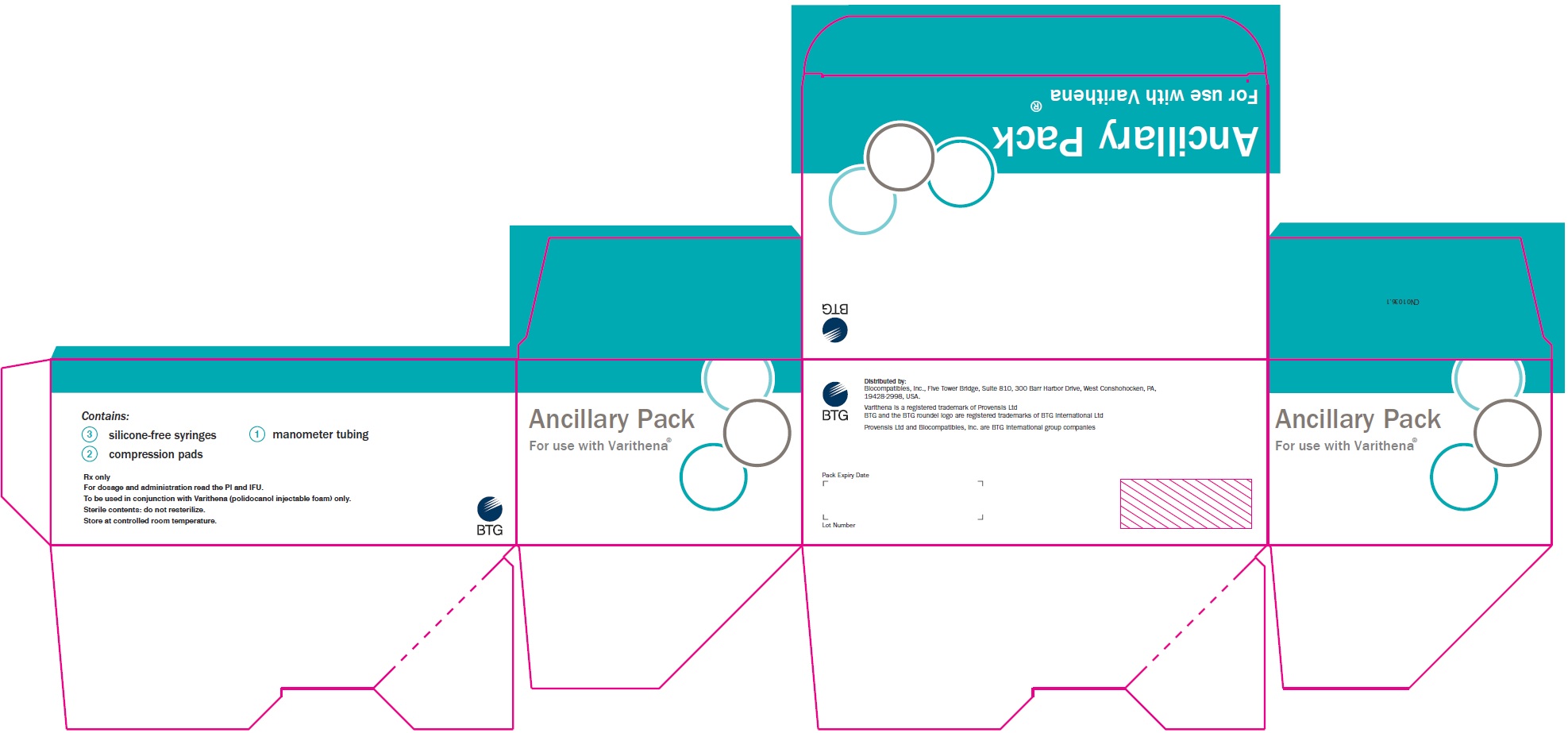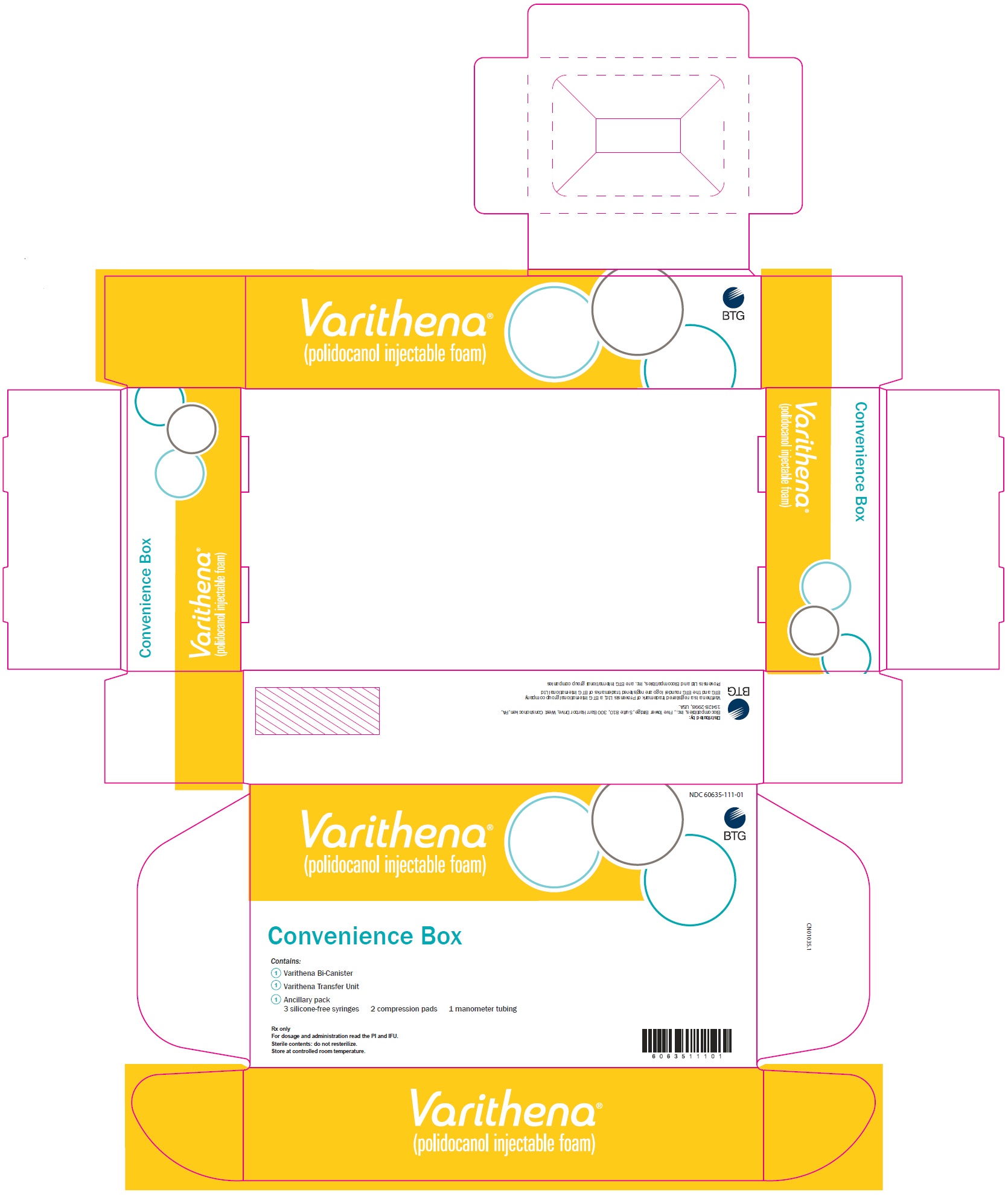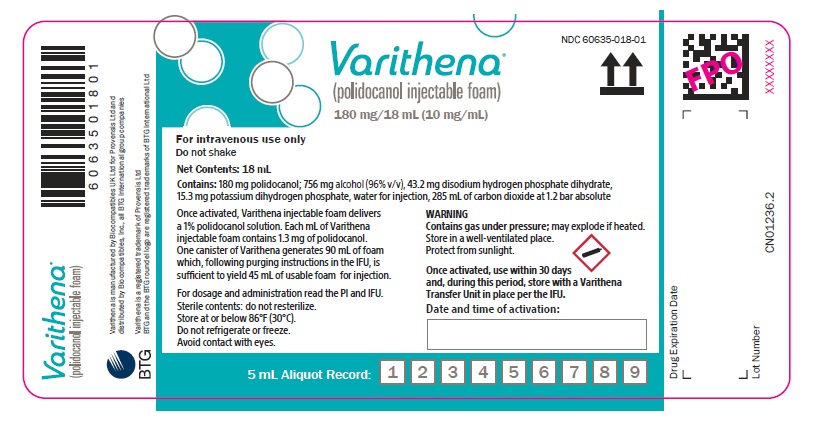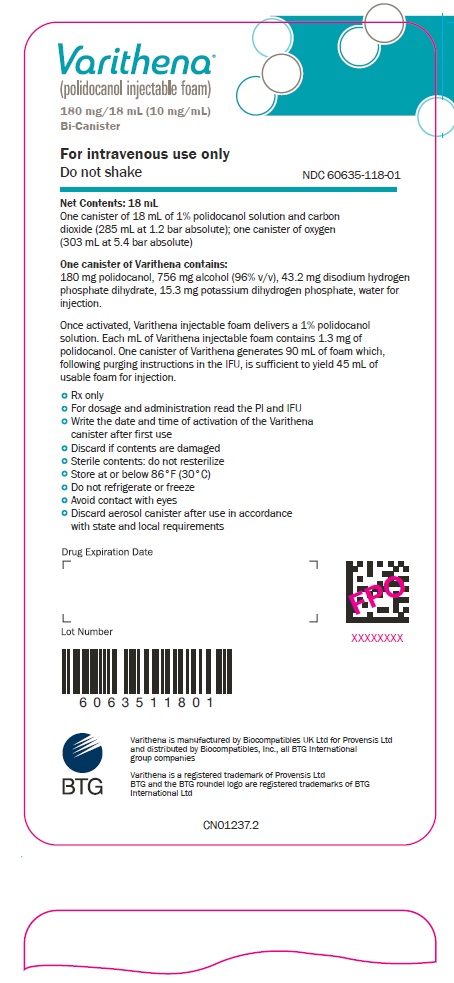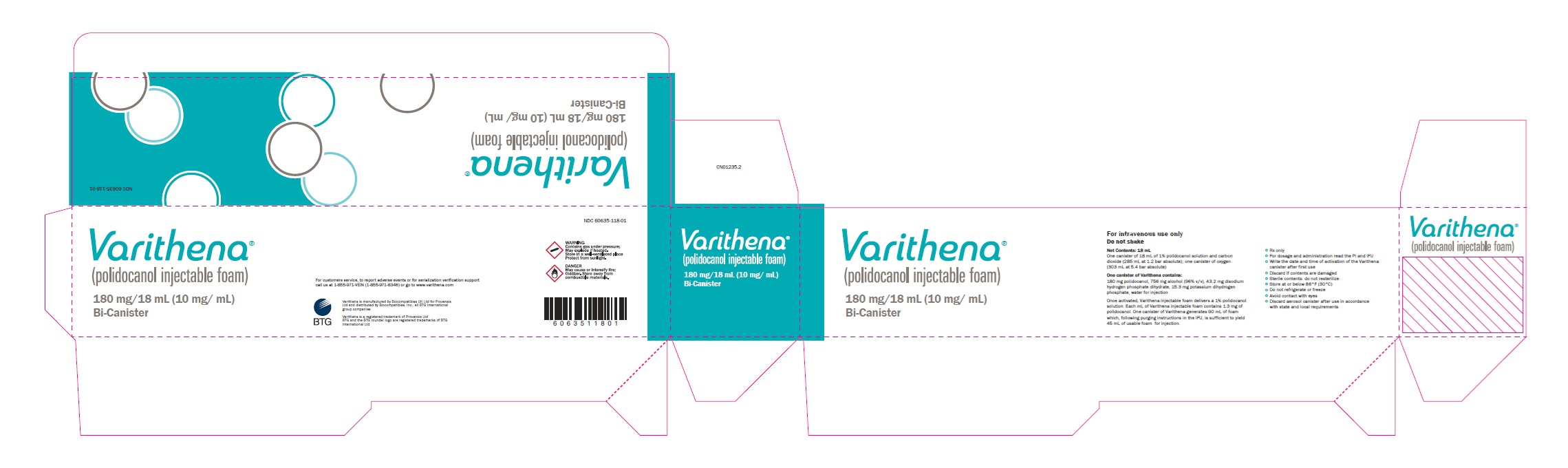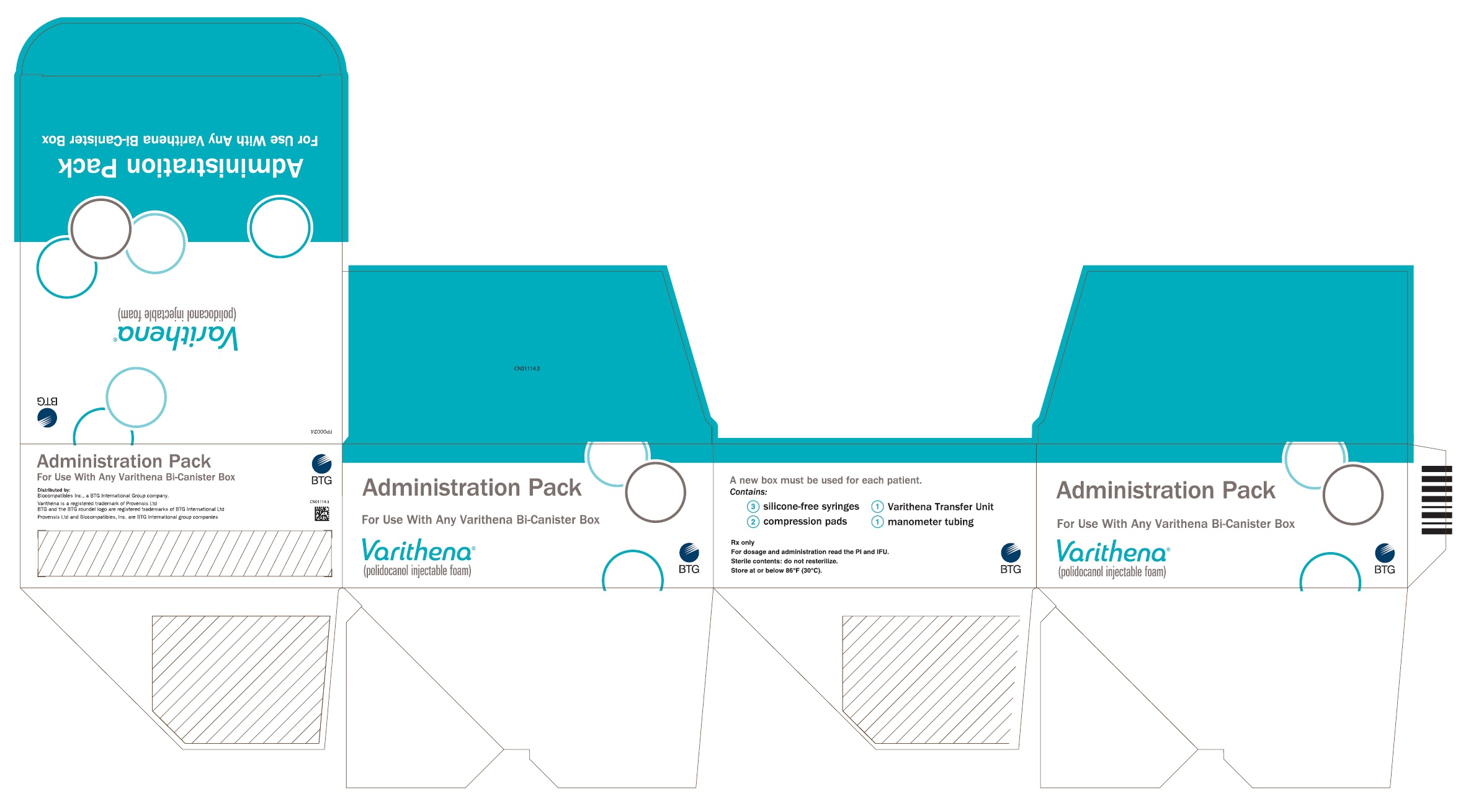 DRUG LABEL: Varithena
NDC: 60635-107 | Form: KIT | Route: INTRAVENOUS
Manufacturer: Biocompatibles, Inc.
Category: prescription | Type: HUMAN PRESCRIPTION DRUG LABEL
Date: 20251124

ACTIVE INGREDIENTS: POLIDOCANOL 10 mg/1 mL
INACTIVE INGREDIENTS: WATER; POTASSIUM PHOSPHATE, MONOBASIC 0.85 mg/1 mL; ALCOHOL 42 mg/1 mL; SODIUM PHOSPHATE, DIBASIC, DIHYDRATE 2.4 mg/1 mL; CARBON DIOXIDE 15.8 mL/1 mL; OXYGEN

HIGHLIGHTS OF PRESCRIBING INFORMATION

These highlights do not include all the information needed to use VARITHENA® safely and effectively. See Full Prescribing Information for VARITHENA.
VARITHENA (polidocanol injectable foam), for intravenous use
Initial U.S. Approval: 2013

1 INDICATIONS AND USAGE

VARITHENA (polidocanol injectable foam) is a sclerosing agent indicated for the treatment of incompetent great saphenous veins, accessory saphenous veins, and visible varicosities of the great saphenous vein (GSV) system above and below the knee. VARITHENA improves the symptoms of superficial venous incompetence and the appearance of visible varicosities. (1).

2 DOSAGE AND ADMINISTRATION

Incompetent great saphenous or accessory saphenous veins: Use Varithena 1% (CEAP Class 2-6 Disease). (2).
For intravenous use which should be performed under ultrasound guidance when treating the GSV.

Use up to 5 mL per injection and 15 mL per treatment session. (2)
Separate treatment sessions by a minimum of 5 days. (2)

3 DOSAGE FORMS AND STRENGTHS

VARITHENA is supplied as polidocanol solution (10 mg/mL) in 18 mL or 7.75 mL; and must be activated before use. (3)

Once activated, VARITHENA is a white, injectable foam delivering the polidocanol solution. (3) Each mL of VARITHENA injectable foam contains 1.3 mg of polidocanol.

4 CONTRAINDICATIONS

- Known allergy to polidocanol (4)
- Acute thromboembolic disease (4)

5 WARNINGS AND PRECAUTIONS

- Be prepared to treat anaphylaxis. (5.1)
- Tissue ischemia and necrosis: do not inject intra-arterially. (5.2)
- Venous Thrombosis. (5.3)

6 ADVERSE REACTIONS

In clinical trials, the most common related adverse events (occurring in ≥3% of patients treated with VARITHENA) were pain/discomfort in extremity, infusion site thrombosis (retained coagulum), injection site hematoma or pain, thrombophlebitis superficial, and extravasation.(6.1)

To report SUSPECTED ADVERSE REACTIONS, contact Biocompatibles, Inc. at 1-855-971-VEIN (1-855-971-8346) or FDA at 1-800-FDA-1088 or www.fda.gov/medwatch.

7 DRUG INTERACTIONS

There are no known drug interactions with VARITHENA. (7)

FULL PRESCRIBING INFORMATION

1 INDICATIONS AND USAGE

VARITHENA (polidocanol injectable foam) is indicated for the treatment of incompetent great saphenous veins, accessory saphenous veins, and visible varicosities of the great saphenous vein (GSV) system above and below the knee. VARITHENA improves the symptoms of superficial venous incompetence and the appearance of visible varicosities.

2 DOSAGE AND ADMINISTRATION

For intravenous use only.

VARITHENA is intended for intravenous injection using ultrasound guidance, administered via a single cannula into the lumen of the target incompetent trunk veins or by direct injection into varicosities. Use up to 5 mL per injection and no more than 15 mL per session.

Physicians administering VARITHENA must be experienced with venous procedures and be trained in the administration of VARITHENA.

Activate VARITHENA using the VARITHENA oxygen canister and polidocanol canister (see Instructions for Use). Once a VARITHENA transfer unit is in place, foam can be generated and transferred to a syringe. Discard the syringe contents if there are any visible bubbles. Administer the injectable foam within 75 seconds of extraction from the canister to maintain injectable foam properties. Use a new sterile syringe after each injection. Use a new VARITHENA transfer unit for each treatment session.

Local anesthetic may be administered prior to cannula insertion but neither tumescent anesthesia nor patient sedation is required. Cannulate the vein to be treated using ultrasound guidance to confirm venous access.

Inject freshly generated VARITHENA injectable foam slowly (approximately 1 mL/second in the GSV and 0.5 mL/second in accessory veins or varicosities) while monitoring using ultrasound. Confirm venospasm of the treated vein using ultrasound.

When treating the proximal GSV, stop the injection when VARITHENA is 3-5 cm distal to the saphenofemoral junction (SFJ).

Apply compression bandaging and stockings and have the patient walk for at least 10 minutes, while being monitored. Maintain compression for 2 weeks after treatment.

Repeat treatment may be necessary if the size and extent of the veins to be treated require more than 15 mL of VARITHENA. Separate treatment sessions by a minimum of 5 days.

Retained coagulum may be removed by aspiration (microthrombectomy) to improve comfort and reduce skin staining.

3 DOSAGE FORMS AND STRENGTHS

VARITHENA is available in the following presentations:

- 180 mg/18 mL (10 mg/mL)
- 77.5 mg/7.75 mL (10 mg/mL)

Once activated, VARITHENA is a white, injectable foam delivering a 1% polidocanol solution.

Each mL of VARITHENA injectable foam contains 1.3 mg of polidocanol

4 CONTRAINDICATIONS

The use of VARITHENA is contraindicated in patients with:

- known allergy to polidocanol [see Warnings and Precautions (5.1)]
- acute thromboembolic disease

5 WARNINGS AND PRECAUTIONS

5.1 Anaphylaxis

Severe allergic reactions have been reported following administration of liquid polidocanol, including anaphylactic reactions, some of them fatal. Observe patients for at least 10 minutes following injection and be prepared to treat anaphylaxis appropriately.

5.2 Tissue Ischemia and Necrosis

Intra-arterial injection or extravasation of polidocanol can cause severe necrosis, ischemia or gangrene Patients with underlying arterial disease, such as marked peripheral arteriosclerosis or thromboangiitis obliterans (Buerger’s Disease) may be at increased risk for tissue ischemia. If intra-arterial injection of polidocanol occurs, consult a vascular surgeon immediately.

5.3 Venous Thrombosis

VARITHENA can cause venous thrombosis [see Adverse Reactions (6)]. Follow administration instructions closely and monitor for signs of venous thrombosis after treatment. Patients with reduced mobility, history of deep vein thrombosis or pulmonary embolism, or recent (within 3 months) major surgery, prolonged hospitalization, or pregnancy are at increased risk for developing thrombosis.

6 ADVERSE REACTIONS

6.1 Clinical Trials Experience

Because clinical trials are conducted under controlled but widely varying conditions, adverse reaction rates observed in clinical trials of VARITHENA cannot be directly compared to rates in the clinical trials of other drugs or procedures and may not reflect the rates observed in practice.

A total of 1333 patients with GSVI in 12 clinical trials were evaluated for safety when treated with VARITHENA at dose concentrations of 0.125%, 0.5%, 1.0%, or 2.0%, including 437 patients treated with VARITHENA in placebo-controlled clinical trials.

Adverse reactions occurring in 3% more patients receiving VARITHENA 1% than receiving placebo are shown in Table 1.

Table 1: Treatment-emergent adverse reactions (3% more on VARITHENA 1% than on
placebo) through Week 8 (n=588)
Adverse Reaction | Placebo (N=151) | VARITHENA 1.0% (N=149)
Pain in extremity | 14 (9.3) | 25 (16.8)
Infusion site thrombosisb | 0 | 24 (16.1)
Contusion/injection site hematoma | 9 (6.0) | 23 (15.4)
Limb discomfort | 5 (3.3) | 18 (12.1)
Tenderness/injection site pain | 5 (3.3) | 16 (10.7)
Venous thrombosis limbc | 0 | 12 (8.1)
Thrombophlebitis superficial | 2 (1.3) | 8 (5.4)
Deep vein thrombosis | 0 | 7 (4.7)
a Retained coagulum.
b Common femoral vein thrombus extension (non-occlusive thrombi starting in the superficial vein and extending into the
common femoral vein).

In VARITHENA-treated patients, 80% of pain events in the treated extremity resolved within 1 week.

Proximal symptomatic venous thrombi occurred in <1% of patients treated with VARITHENA. Approximately half of patients with thrombi received treatment with anticoagulants.

Since VARITHENA induces thrombosis in the treated superficial veins, D-dimer is commonly elevated post-treatment and is not useful diagnostically to assess patients for venous thrombus following treatment with VARITHENA.

Neurologic adverse events (cerebrovascular accident, migraines) have been reported in patients following administration of physician compounded foam sclerosants. None of the 1333 patients in the VARITHENA trials experienced clinically important neurological or visual adverse events suggestive of cerebral gas embolism. The incidence of neurologic and visual adverse events within 1 day of treatment in the placebo-controlled studies was 2.7% in the pooled VARITHENA group and 4.0% in the placebo groups.

Skin discoloration adverse events were reported in 1.1% of the pooled VARITHENA group and 0.7% of the placebo group in the placebo-controlled studies.

7 DRUG INTERACTIONS

No specific drug interaction studies have been performed. There are no known drug interactions with VARITHENA.

8 USE IN SPECIFIC POPULATIONS

8.1 Pregnancy

Risk Summary

Few published case reports with use of polidocanol-containing products, including VARITHENA, in pregnant women have not identified any drug-associated risk for major birth defects, miscarriage, or adverse maternal or fetal outcomes. Although no risks have been identified, there is minimal benefit in treating lower extremity varicosities during pregnancy and lower extremity varicosities that develop during pregnancy as they may spontaneously regress postpartum. In animal reproduction studies, no adverse developmental effects were observed with intravenous administration of polidocanol to pregnant rats and rabbits during organogenesis at dose levels up to approximately 13.5 and 12 times, respectively, the proposed maximum human dose of 15 mL of 1% VARITHENA based on body surface area (see Data).

The estimated background risk of major birth defects and miscarriage for the indicated population is unknown. All pregnancies have a background risk of birth defect, loss, or other adverse outcomes. In the U.S. general population, the estimated background risk of major birth defects and miscarriage in clinically recognized pregnancies is 2 to 4% and 15 to 20%, respectively.

Data
Animal Data

Developmental reproductive toxicity testing was performed in rats and rabbits using intravenous administration of polidocanol solution. In rabbits, dose levels up to and including 10 mg/kg/day (approximately 12 times the proposed maximum human dose of 15 mL of 1% VARITHENA based on body surface area) did not produce any indication of adverse effects on embryo-fetal mortality, fetal weight, or the incidences of fetal abnormalities and variants. In rats administered 27 mg/kg/day of polidocanol solution (approximately 13.5 times the human dose based on body surface area), there were no adverse effects on pregnancy performance or fetal development. In a peri-natal and post-natal study in rats, dose levels of polidocanol up to 9 mg/kg/day (approximately 4.5 times the human dose based on body surface area) were without effects on the development of the conceptus and offspring, and at a dose level of 27 mg/kg/day of polidocanol solution (approximately 13.5 times the human dose based on body surface area), effects were confined to an equivocal reduction in body weights of first-generation males, and an associated equivocal delay in the age of preputial separation.

8.2 Lactation

Risk Summary

There are no data on the presence of polidocanol in human milk, the effects on the breastfed infant, or the effects on milk production. A lactating woman may consider interrupting breastfeeding and pumping anddiscarding breast milk up to 8 hours after VARITHENA administration in order to minimize exposure to a breastfed infant.

8.4 Pediatric Use

Safety and effectiveness in pediatric patients have not been established.

8.5 Geriatric Use

Of the 1333 subjects in clinical studies treated with VARITHENA, 9.1% (n=121) were ≥65 years of age. No clinically important differences in safety or efficacy were observed between older and younger patients in all studies.

10 OVERDOSAGE

There are no known cases of overdosage with VARITHENA. In clinical studies, total volumes of up to 60 mL of VARITHENA per treatment session have been administered.

11 DESCRIPTION

VARITHENA injectable foam contains the sclerosant, polidocanol. It is intended for intravenous use only.

Chemically, polidocanol is polyoxyl lauryl ether. The structural formula is represented below:

Polidocanol has the molecular formula CH3(CH2)11(OCH2CH2)nOH and a molecular weight of 582.9 when the average ethylene glycol moieties is nine (n=9). Polidocanol is a white to almost white, waxy, hygroscopic solid that is soluble in water and alcohol and melts at temperatures above 20°C.

VARITHENA is a sterile, injectable foam of an aqueous polidocanol solution (1%) containing the following inactive ingredients: alcohol (4.2% w/w, purity 96% v/v) disodium hydrogen phosphate dihydrate (0.24% w/w), and potassium dihydrogen phosphate (0.085% w/w) with a pH of 6.0-7.5.

The injectable foam is generated after activation of the polidocanol canister with oxygen from a second aluminum canister, resulting in a final gas mixture of oxygen:carbon dioxide in a ratio of 65:35 with low (<0.8%) nitrogen content. At the time of use, VARITHENA is generated as an injectable foam of controlled density and bubble size. The foam is then transferred to a syringe through the VARITHENA transfer unit. The injectable foam has a liquid to gas ratio of approximately 1:7 by volume. The median bubble diameter is less than 100 µm and no bubbles are greater than 500 µm.

12 CLINICAL PHARMACOLOGY

12.1 Mechanism of Action

VARITHENA is a drug/device combination product that generates injectable foam. The injectable foam is composed of a liquid and gas phase, both of which are necessary to have its therapeutic effect. VARITHENA is intended to act as follows: (1) the foam displaces blood from the vein to be treated, and (2) the polidocanol then scleroses the endothelium.

The active pharmaceutical ingredient of VARITHENA is polidocanol, a non-ionic surfactant sclerosing agent. The hydrophobic pole of the polidocanol molecule attaches to the lipid cell membrane of the venous endothelium, resulting in disruption of the osmotic barrier, destruction of the venous endothelium, and vasospasm. Following exposure to polidocanol, the interior surface of the vein becomes thrombogenic, which leads to thrombus formation and venous occlusion. The occluded vein is eventually replaced by fibrous connective tissue. Polidocanol is deactivated upon contact with blood, thus limiting the sclerosant action to the endothelium near the site of injection.

12.2 Pharmacodynamics

The active pharmaceutical ingredient in VARITHENA is polidocanol. Polidocanol damages the endothelium of blood vessels.

12.3 Pharmacokinetics

The pharmacokinetics of VARITHENA (as a weighted sum of 4 oligomers: E5, E9, E12 and E14) were evaluated at two concentrations (1% and 2%) randomly assigned within gender in 20 patients with GSV incompetence.

When administered as an intravenous injectable foam as two fixed 5 mL doses separated by 10 minutes, polidocanol was rapidly detected in plasma, reaching maximum concentration of drug in the body after dosing (Cmax) within 15 minutes of the first injection and within 5 minutes of receiving the second injection of VARITHENA 1% or VARITHENA 2%. The mean volume of distribution (Vd) of polidocanol ranged from 35 to 82 L.

Mean systemic clearance (CL) of polidocanol ranged from 0.2 to 0.4 L/min. The clearance of E5 was significantly greater than that of longer oligomers. Mean terminal elimination half-life (t1/2) ranged from 102 to 153 minutes, with most plasma samples below the limit of quantitation (BLQ) at the end of the 8-hour collection period. The increase in plasma polidocanol concentrations was less than proportional with increasing VARITHENA concentration. Weight-normalized data demonstrated no consistent differences in Cmax or AUC between males and females.

13 NONCLINICAL TOXICOLOGY

13.1 Carcinogenesis, Mutagenesis, Impairment of Fertility

Long-term studies in animals have not been performed to evaluate carcinogenic potential of VARITHENA. No mutagenic activity was observed in the in vitro bacterial reverse mutation assay at non-toxic concentrations. No mutagenic activity was observed in the in vitro mouse lymphoma assay in the absence of S9 mix and was weakly mutagenic in the presence of S9 close to the limit of acceptance for the accompanying level of toxicity. No micronucleus induction was detected in the in vivo assay on mouse bone marrow cells up to the maximum tolerated dose of 80 mg/kg.

There was no adverse effect on fertility in both male and female rats at 27 mg/kg/day. This dose level is approximately 13.5 times the proposed maximum human dose based on body surface area.

13.2 Animal Toxicology and/or Pharmacology

The pharmacological effects of polidocanol solution on the renal function of the rat were evaluated and at the highest dose tested (10 mg/kg) hematuria occurred in 67% of animals. This dose is 5 times higher than the proposed maximum human dose based on body surface area. Blood was no longer detectable in urine 24 hours after dosing. In the 28-day repeated dose toxicity study in rat blood, pigments were noted in the urine for animals in all treatment groups, including male controls, at the end of the 4-week treatment period with up to 27 mg polidocanol/kg/day. Following the 2-week recovery period, there was still evidence that blood pigments were present in the urine but the incidence and severity was decreased when compared to the main study animals. There were no histopathological findings in the urinary bladder in any study animals.

In a cardiovascular pharmacology study in the anesthetized dog at 20 mg/kg (approximately 33 times the human dose based on body surface area), statistically significantly higher values for P-Q interval were measured before and during dosing and at all time points up to 30 minutes after dosing. An increase in QRS interval was also measured after dosing of 20 mg/kg and at 5 and 10 minutes after dosing. This effect was short lived and was no longer seen at 15 minutes after dosing. In addition, there was an increase in diastolic pressure with increasing dose of polidocanol. This increase became significantly greater (p<0.05) than baseline before injection of the final and highest dose (20 mg/kg).

In a further cardiovascular pharmacology study conducted with a once weekly, for four weeks, intravenous bolus injection of VARITHENA in the conscious dog, dose levels of up to 8.0 mL/kg (approximately 17 times the human dose based on body surface area) to beagle dogs caused only a transient, but consistent, effect on respiration, evidenced by a decrease in tidal volume and RMV at 15 minutes post-dose, resolving by one hour post-dose. Histopathology of the lung at the end of the 3-month follow-up period showed no abnormalities.

14 CLINICAL STUDIES

VARITHENA was evaluated in two randomized, blinded, multicenter clinical trials designed to assess the efficacy and safety of VARITHENA 0.5%, 1.0%, and 2.0% (VANISH-1) and VARITHENA 0.5% and 1.0% (VANISH-2) compared with placebo in the treatment of both symptoms and appearance in patients with SFJ incompetence as evidenced by reflux of the GSV or major accessory veins. In both studies, a VARITHENA 0.125% treatment group was included as a control for blinding of the duplex ultrasound assessment. Patients with history of deep vein thrombosis or pulmonary embolism; inability to comply with post-treatment compression due to severe peripheral arterial disease or leg obesity; incompetence of the small saphenous vein or deep venous reflux as a major source of reflux; or reduced mobility, major surgery, pregnancy, or prolonged hospitalization within 3 months were excluded. Patients were randomized in an equal distribution to each treatment group; the primary time point for analyses of the primary, secondary, and tertiary efficacy endpoints was Week 8.

In these clinical trials, the maximum volume of injectable foam or placebo to be administered per treatment session was 15 mL.

In VANISH-1, patients received one blinded treatment and in VANISH-2, patients received one blinded treatment with an option for a second blinded treatment 1 week later. In VANISH-2, patients in the VARITHENA 1.0% treatment group received an average of 1.4 blinded treatments. All patients received post-procedure compression therapy for 14 days following treatment.

Of the 519 patients randomized into VANISH-1 and VANISH-2, a total of 511 were treated with either VARITHENA 0.5% (n=111), 1.0% (n=110), or 2.0% (n=63), VARITHENA 0.125% as control (n=114), or placebo (n=113). Ninety-nine percent of the patients in VANISH-1 and VANISH-2 completed the blinded treatment period.

In the VARITHENA 1% group in VANISH-2, 23 of 58 patients received an additional blinded treatment. Two of these patients had retreatment of veins treated in the initial treatment session. The remaining 21 patients received treatment for additional veins not treated in the initial treatment session.

The mean age was approximately 50 years and approximately three-fourths of the patients were women. The mean BMI was similar in VANISH-1 and VANISH-2, at 28 kg/m^2 (range 16 to 44 kg/m^2) and 30 kg/m^2 (range 17 to 48 kg/m^2), respectively. The mean baseline GSV diameter was also similar in VANISH-1 and VANISH-2, at 7.6 mm (range 1.5 to 25.9 mm) and 8.7 mm (range 3.1 to 19.4 mm), respectively. Overall, 22% of patients in VANISH-1 and 25% of patients in VANISH-2 reported one or more prior varicose vein procedures in the leg to be treated.

For both clinical trials, the primary efficacy endpoint was improvement in patient symptoms, as measured by the change from baseline to Week 8 in the 7-day average electronic daily diary VVSymQ® score. The VVSymQ® score is a patient-reported outcome measure based on daily patient assessment of the varicose vein symptoms determined to be most important to patients: heaviness, achiness, swelling, throbbing, and itching. VVSymQ® scores range from 0 to 25, where 0 represents no symptoms and 25 represents all 5 symptoms experienced all of the time. Results are shown in Table 2.

For both VANISH-1 and VANISH-2, treatment with 1.0% was superior to placebo in improving symptoms as measured by VVSymQ®, when either a duration or an intensity scale was used to measure patients’ symptoms.

Table 2: Improvement in Symptoms of Varicose Veins as Measured by VVSymQ® at Week 8, VANISH-1 and VANISH-2
 | VVSymQ®
 | VANISH-1 |  | VANISH-2
 | Placebo | VARITHENA 1.0% | Placebo | VARITHENA 1.0%
N | 55 | 50 | 54 | 57
Baseline score, mean | 8.60 | 8.82 | 9.26 | 7.82
Adjusted mean change from baseline at week 8 | -2.13 | -4.87 | -2.00 | -5.06
Clinically meaningful improvement in symptoms at week 8* | 5.4% (n=56) | 64.7% (n=51) | 19.6% (n=56) | 75.9% (n=58)
Comparison vs. Placebo at week 8, p-value, adjusted mean change |  | <0.0001 |  | <0.0001
*Percent of patients who reported their symptoms had "moderately improved" or "much improved" compared with baseline.

The co-secondary endpoints in VANISH-1 and VANISH-2 were the improvement in appearance of visible varicosities from baseline to Week 8 as measured by 1) patients scoring the appearance of their varicose veins in the medial view of their study leg (PA-V^3 score) from "Not at all noticeable" (a score of 0) to "Extremely noticeable" (a score of 4); and 2) an independent photography review panel rating the severity of the patient's varicose vein appearance in standardized digital photographs of the medial view of each patient's study leg (IPR-V^3 score) from "None" (a score of 0) to "Very severe" (a score of 4). Results are shown in Table 3.

Table 3: Improvement in Appearance of Visible Varicosities as Measured by IPR-V^3and PA-V^3at Week 8, VANISH-1 and
VANISH-2
 | VANISH-1 |  | VANISH-2
 | Placebo | VARITHENA 1.0% | Placebo | VARITHENA 1.0%
IPR-V^3
n | 55 | 49 | 56 | 57
Baseline score, mean | 1.82 | 1.98 | 2.18 | 2.02
Adjusted mean change from baseline at week 8 | -0.01 | -0.76 | -0.07 | -0.83
Clinically meaningful improvement in appearance at week 8† | 8.9% (n=56) | 70.6% (n=51) | 0 (n=56) | 70.7% (n=58)
Comparison vs. Placebo, p-value at week 8, adjusted mean change |  | <0.0001 |  | <0.0001
PA-V^3
N | 55 | 50 | 56 | 57
Baseline score, mean | 3.49 | 3.46 | 3.30 | 3.49
Adjusted mean change from baseline at week 8 | -0.15 | -1.60 | -0.32 | -1.79
Clinically meaningful improvement in appearance at week 8† | 3.6% (n=56) | 54.9% (n=51) | 7.1% (n=56) | 69.0% (n=58)
Comparison vs. Placebo, p-value at week 8, adjusted mean change |  | <0.0001 |  | <0.0001
†Percent who reported the appearance of varicose veins had “moderately improved” or “much improved” compared with
baseline.

Tertiary endpoints in VANISH-1 and VANISH-2 included response to treatment as determined by change from baseline in Venous Clinical Severity Score (VCSS), by duplex ultrasound, and by change from baseline in Venous Insufficiency Epidemiologic and Economic Study – Quality of Life/Symptoms (VEINES-QOL) score.

VCSS is a clinician rating of severity of chronic venous insufficiency ranging from 0 to 30, where higher scores indicate more severe venous disease. In VANISH-1 and VANISH-2, the adjusted mean changes from baseline in VCSS in the 1% VARITHENA treatment groups were 3.70 and 5.05, respectively, at Week 8 compared with 0.75 and 1.52 points in the placebo groups, respectively. For both studies, the differences between these improvements are statistically significant (P<0.0001).

The physiological response to treatment as measured by duplex ultrasound (duplex response) was defined as elimination of reflux through the SFJ and/or complete occlusion of all incompetent GSV and major accessory veins at baseline. The primary comparison for duplex response in both studies was the pooled VARITHENA groups versus the VARITHENA 0.125% (control) group. Results are shown in Table 4.

Table 4: Response to Treatment as Measured by Duplex Ultrasound at Week 8, VANISH-1 and VANISH-2
Parameter | Treatment Group, %
 | Placebo | VARITHENA 0.125% (control) | VARITHENA 1.0%
Responders, VANISH-1* | 5.4% (n=56) | 42.1% (n=57) | 80.4% (n=51)
Responders, VANISH-2 | 1.8% (n=56) | 59.6% (n=57) | 86.2% (n=58)
*In VANISH-1, a significant dose-response trend was evident between the percent of responders and the dose concentration of VARITHENA (P<0.0001).

VEINES-QOL is a disease-specific quality of life instrument, ranging from 0 (worst possible quality of life) to 100 (best possible quality of life). In VANISH-1 and VANISH-2, the adjusted mean changes from baseline in VEINES-QOL in the pooled VARITHENA treatment groups were 21.2 and 21.6, respectively, at Week 8 compared with 7.7 and 7.4 points in the placebo groups, respectively. For both studies, the differences between these improvements are statistically significant (P<0.0001).

For efficacy endpoints, VARITHENA treatment effects were consistent across subgroups of age, sex, BMI (up to 48 kg/m^2), CEAP clinical class, GSV diameter (up to 25.9 mm), and VCSS.

16 HOW SUPPLIED/STORAGE AND HANDLING

16.1 How Supplied

VARITHENA (polidocanol injectable foam) product is available in four configurations, each containing two sterile, connected, 303-mL aluminum alloy cylinders, one containing polidocanol solution (10 mg/mL) under carbon dioxide, and the other containing pressurized oxygen.

Polidocanol mg | Usable foam mL | Administration Pack |  | NDC
Polidocanol mg | Usable foam mL | Transfer units | Ancillary Pack* | NDC
77.5 | 15 | 0 | 0 | 60635-107-01 PD Canister - 60635-007-01
77.5 | 15 | 1 | 1 | 60635-111-01 PD Canister - 60635-007-01
180 | 45 | 0 | 0 | 60635-118-01 PD Canister - 60635-018-01
180 | 45 | 3 | 3 | 60635-133-01 PD Canister - 60635-018-01
*Ancillary Pack includes three 10-mL syringes, one 20-inch manometer tube, and two compression pads.

16.2 Storage and Handling

Do not shake VARITHENA canisters.

Avoid contact with eyes.

Store the VARITHENA Bi-Canister or convenience box at or below 86°F (30°C);

Do not refrigerate or freeze.

Unused, non-activated VARITHENA canisters may be stored in the flat or upright position.

Contains gas under pressure: May explode if heated. Store in a well-ventilated place. Store the canisters away from sources of heat including strong light conditions.

Pressurized Oxygen: May cause or intensify fire; oxidizer. Store away from combustible materials.

Once activated, the canister of 180 mg/18 mL (10 mg/mL) VARITHENA must be used within thirty (30) days.

Once activated, the canister of 77.5mg/7.75mL (10mg/mL) VARITHENA must be used within thirty (30) days.

Store activated canisters of VARITHENA upright, with the VARITHENA transfer unit attached, under the same temperature conditions as the VARITHENA Bi-Canister or convenience box. Use a new VARITHENA transfer unit for each treatment session.

Discard aerosol canisters after use in accordance with state and local requirements.

For more information, please refer to the IFU.

17 PATIENT COUNSELING INFORMATION

Advise the patient to keep post-treatment bandages dry and in place for 48 hours and to wear compression stockings on the treated legs continuously for 2 weeks. Compression stockings should be thigh high or knee high, depending upon the area treated, in order to provide adequate coverage. Advise the patient to walk for at least 10 minutes immediately after the procedure and daily for the next month. Following treatment, advise the patient to avoid heavy exercise for 1 week and extended periods of inactivity for 1 month.

If you would like more information, please talk with your doctor. For more information about VARITHENA, you can also call us at 1-855-971-VEIN (1-855-971-8346) or go to www.VARITHENA.com.

Manufactured for Provensis Ltd by:

Biocompatibles UK Ltd

Chapman House, Weydon Lane, Farnham, UK, GU9 8QL

Distributed by:

Biocompatibles Inc.,

Provensis Ltd, Biocompatibles UK Ltd, and Biocompatibles, Inc. are BTG International group companies

VARITHENA and VVSymQ are registered trademarks of Provensis Ltd

BTG and the BTG roundel logo are registered trademarks of BTG International Ltd

Tyvek is a registered trademark of E. I. du Pont de Nemours and Company

CN01241.4

INSTRUCTIONS FOR USE

VARITHENA Delivery System

Instructions for Use

Please read all prescribing information before using the product.

Rx Only

The Instructions for Use are for the entire VARITHENA system. There are 4 packaging configurations:

180 mg/18 mL Configuration:

Option A: Bi-Canister box and Administration Pack*

Option B: Convenience box (Bi-Canister Box + 3 Ancillary Packs + 3 VARITHENA transfer units)*

*The components in each packaging configuration are to be used only in conjunction with each other for activation of VARITHENA.
Administration Packs can be used for either configuration for further treatment sessions.

180 mg/18 mL Configuration: Always write the activation date and time on the canister and verify the product has not expired prior to use. Once the VARITHENA canister has been activated, the shelf life for the product is thirty (30) days.

A canister of VARITHENA generates 90 mL of foam which, following purging instructions contained in this IFU, is sufficient to yield 45 mL of usable foam for injection. The gas mix of the foam is 65:35 O2: CO2.

77.5 mg/7.75 mL Configuration:

Option A: Bi-Canister box and Administration Pack*

Option B: Convenience box (Bi-Canister Box + 1 Ancillary Pack + 1 VARITHENA transfer unit)*

*The components in each packaging configuration are to be used only in conjunction with each other for activation of VARITHENA.

77.5 mg/7.75 mL Configuration:Always write the activation date and time on the canister and verify the product has not expired prior to use. Once the VARITHENA canister has been activated, the shelf life for the product is thirty (30) days.

A canister of VARITHENA generates 30 mL of foam which, following purging instructions contained in this IFU, is sufficient to yield 15 mL of usable foam for injection. The gas mix of the foam is 65:35 O2: CO2.

WARNINGS:

As the foam fills the syringe and before injecting, inspect the syringe full of foam for any visible bubbles. If there are any present, the foam should be emptied into the VARITHENA transfer unit waste chamber and the syringe refilled.

Do not shake VARITHENA canisters.

Always use a fresh pair of sterile gloves when handling the Bi-Canister and VARITHENA transfer unit.

Notes: Use a new sterile syringe after each injection. Never fill a syringe until just before the foam is required.

Use foam within 75 seconds of generation or discard and generate new foam.

The activated VARITHENA canister should always be stored with a VARITHENA transfer unit in place in the upright position at or below 86°F (30°C) - do not refrigerate or freeze, in an appropriately controlled clean area to limit contamination. A new VARITHENA transfer unit must be used for each treatment session.

Unpacking VARITHENA:

Option A for 180 mg/18 mL: Bi-Canister Box and Administration Pack

Option A for 77.5 mg/7.75 mL: Bi-Canister Box and Administration Pack

Gather all the items needed for the generation of foam: the VARITHENA Bi-Canister box (Figure 1a), Administration Pack (including: VARITHENA transfer unit, manometer tube, compression pad and silicone-free syringes) (Figure 1b), and the following items that are not supplied: scissors, pen, sterile alcoholic wipes, timer and gloves (Figure 1c).

Open the VARITHENA Bi-Canister box and remove the VARITHENA Bi-Canister pouch. Open the Administration Pack and remove the components. Inspect the pouch and components for damage (do not use product if there are any visible signs of damage to pouch or components).

Unpacking VARITHENA:

Option B for 180 mg/18 mL Product: Convenience Box (Bi-Canister Box + 3 Ancillary Packs + 3 VARITHENA transfer units)

Gather all the items needed for the generation of foam: the VARITHENA Bi-Canister Box) (Figure 2a), Ancillary Pack (including silicone-free syringes, manometer tubing, and compression pads (Figure 2b) and VARITHENA transfer unit (Figure 2c), and the following items that are not supplied: scissors, pen, sterile alcoholic wipes, timer and gloves (Figure 2d).

Open the VARITHENA Convenience box and remove all the components. Open the VARITHENA Bi-Canister box and remove the VARITHENA Bi-Canister pouch. Open an Ancillary Pack and remove the components. Inspect the pouch and components for damage (do not use product if there are any visible signs of damage to pouch or components).

Unpacking VARITHENA:

Option B for 77.5 mg/7.75 mL product: Convenience Box (Bi-Canister Box + 1 Ancillary Pack + 1 VARITHENA transfer unit)

Gather all the items needed for the generation of foam: the VARITHENA Bi-Canister Box (Figure 3a), Ancillary Pack (including silicone-free syringes, manometer tubing, and compression pads (Figure 3b) and VARITHENA transfer unit (Figure 3c), and the following items that are not supplied: scissors, pen, sterile alcoholic wipes, timer and gloves (Figure 3d).

Open the VARITHENA Convenience box and remove all the components. Open the VARITHENA Bi-Canister box and remove the VARITHENA Bi-Canister pouch. Open the Ancillary Pack and remove the components. Inspect the pouch and components for damage (do not use product if there are any visible signs of damage to pouch or components).

Preparing the Patient

Preparations for treating the patient with VARITHENA should include the following steps:

- Position the patient comfortably on the treatment table in a supine position with their hip externally rotated to facilitate access to the GSV.
- Use ultrasound to find the best site for venous access.
- Using an aseptic technique, infiltrate the skin over the venous access point with local anesthetic.
- Obtain venous access under ultrasound guidance.
- IV catheters that are 16 to 22 gauge and 40 - to 50 - mm long or micropuncture sets are recommended for venous access.
- Prefill the manometer tube with sterile heparinized normal saline solution and connect to the IV catheter.
- Confirm venous access by aspirating with a syringe, blood should be dark and under low pressure.
- Flush the IV catheter and manometer tube with heparinized normal saline and secure it to the skin with adhesive tape, leave the saline syringe connected.
- With the IV catheter in place and secure, place the patient supine and elevate the leg to approximately 45 degrees.

Complete all preparation of the patient and preparations for VARITHENA injectable foam injection before generation of the foam.

VARITHENA Preparation

1 Wearing appropriate sterile gloves, open Bi-Canister pouch using a pair of scissors. Place canisters upright on a cleaned (sterile wipes) stable surface with the white oxygen canister on top (Figure 4). Discard empty pouch.

2 Remove the safety clip by lifting one corner of the clip out (Figure 5). Discard the safety clip.

Gas Activation of the VARITHENA Canistern

3 To begin the gas transfer, twist the canisters together clockwise (Figure 6) until they come to a stop and the small indicators/marks on the collars are aligned (Figure 7). You may hear a bubbling sound.

While the canisters are activating, keep them upright on the clean flat surface for 1 minute. Use a timing device to keep track of the 1 minute time. Extended gassing periods (more than 10 minutes) are undesirable.

4 Note: In order to maintain sterility of the VARITHENA transfer unit, the following steps must be followed. While waiting 1 minute for the gas transfer, open a new VARITHENA transfer unit, blister pack, but leave the VARITHENA transfer unit in the package (Figure 8).

The manometer tubing (20 inch) should have been previously filled with sterile heparinized normal saline solution.

5 After 1 minute,

- Twist the two canisters by turning them in the opposite direction (counterclockwise) as before (Figure 9).
- Pull straight up to separate the oxygen canister from the VARITHENA canister, as shown (Figure 10). Do not separate canisters until you have a VARITHENA transfer unit ready to place onto the VARITHENA canister (See step 6).
- Put the oxygen canister (with white collar) aside.
- The VARITHENA canister (with blue collar) should remain on a clean flat surface, in the upright position.

Write today’s date and time in the “Date and Time of Activation” box on the VARITHENA canister (Figure 11)

Connecting a new VARITHENA transfer unit and syringe

6 Remove the VARITHENA transfer unit from the blister pack, wearing a fresh pair of sterile gloves. Make sure not to touch the sterile underside of the VARITHENA transfer unit, (discard VARITHENA transfer unit if contaminated).

Immediately place the VARITHENA transfer unit on top of the blue VARITHENA canister. Gently rotate the VARITHENA transfer unit clockwise as indicated (Figure 12) until it drops into the collar threads then twist the VARITHENA transfer unit (clockwise) until it reaches a stop (Figure 13).

The system is now activated and ready for use.

7 Once all preparations for injection are complete, i.e., cannula in situ, patient’s leg elevated and a good ultrasound view of the saphenofemoral junction (SFJ) obtained, foam may be generated for immediate use.

Open a sterile 10 mL silicone-free syringe blister pack and keep it in the package until needed.

Remove the syringe from the package, and connect it to the VARITHENA transfer unit as shown (Figure 14).

Priming a New Syringe

8 Gently press down the VARITHENA transfer unit to begin producing foam (Figure 15).

Using continuous pressure, allow the silicone-free syringe to fill between 3 mL and 5 mL.

Release the pressure on the VARITHENA transfer unit and leave the syringe connected.

9 Push the silicone-free syringe plunger in fully to discard its contents (Figure 16). Do not disconnect the syringe.

Note: The foam will automatically be diverted into the waste chamber within the VARITHENA transfer unit (Figure 17). This process eliminates the small quantity of air in the syringe and VARITHENA transfer unit.

Generation of Foam

10 Foam Generation: The technique to produce usable foam requires a single purge cycle before filling the syringe, a process that takes less than 1 second.

Important Note: Foam must be generated by pushing down on the VARITHENA transfer unit continuously without pulling back on the plunger of the syringe (aspirating).

While holding the silicone-free syringe plunger in place, gently press down on the VARITHENA transfer unit to begin the purge cycle (Figure 18).

Visually inspect the flowing foam inside the VARITHENA transfer unit to make sure the visible air bubbles have been expelled (less than 1 second) before releasing the syringe plunger and allowing it to fill to the desired volume (Figure 19).

Draw up to 5 mL of foam into the syringe.

Inspecting and Injecting Foam

11 After the silicone-free syringe has filled to the desired volume, wait 10 seconds to allow the pressure to equalize before removing the syringe from the VARITHENA transfer unit (Figure 20).

WARNING: As the foam fills the syringe and before injecting, inspect the syringe full of foam for any visible bubbles (easily seen with the unaided eye at arm’s length). If there are any present, empty the foam into the VARITHENA transfer unit waste chamber and refill the syringe.

12 Remove the syringe from the VARITHENA transfer unit and inspect it for visible bubbles (Figure 21).

If no visible bubbles are present then the foam is ready for use.

Use the foam within 75 seconds of generation or discard and generate new foam.

WARNING: The total amount of foam injected in any one treatment session must not exceed 15 mL, comprised of individual injections of up to 5 mL each.

After each treatment session, mark-off on the canister label the number of aliquots of up to 5 mL of usable foam drawn from the canister per step 11 (Figure 22).

13 Connect a syringe of freshly generated foam to the manometer tubing, which is already connected to the cannula, in preparation for the initial injection. The manometer tubing (20) inch should have been previously filled with sterile heparinized normal saline solution.

14 Inject the foam at approximately 0.5 mL to 1.0 mL per second through the manometer tubing. Five (5) mLs of foam should be injected in approximately 10 seconds. Always inspect the foam as it passes through the manometer tubing for visible bubbles (Figure 23). If any visible bubbles are seen (easily seen with the unaided eye at arm's length) they should be aspirated back into the silicone-free syringe and the syringe contents discarded back into the VARITHENA transfer unit waste chamber, and a fresh syringe of foam generated.

Notes: Use a new sterile syringe after each injection.

WARNING: The total amount of foam injected in any one treatment session must not exceed 15 mL, comprised of individual injections of up to 5 mL each

Do not remove VARITHENA transfer unit if the VARITHENA canister is to be stored (see Storage)

Change sterile gloves appropriately, to limit any contamination of the VARITHENA transfer unit and Bi-Canister.

Compression Pads

15 Once treatment is complete, the Compression Pads should be used:

The objective of the pads is to focus the compression forces on the treated vein to keep them as free from blood as possible, thus minimizing retained thrombus.

The compression pads supplied should be placed along the course of the treated trunk vein in the thigh, and over raised treated varicose veins above and below the knee. The pads may be shaped to follow the course of the veins. The pads should be placed outside the first layer of limited stretch bandage and held in place by a second layer of bandage.

The appropriate length compression stocking is then applied.

Replacing the VARITHENA Transfer Unit

Important Note: Do not replace the VARITHENA transfer unit if the canister is to be stored for future use. The activated VARITHENA canister should always be stored in an appropriately cleaned area with a VARITHENA transfer unit in place in the upright position at or below 86°F (30°C), do not refrigerate or freeze. Replace the VARITHENA transfer unit just prior to the next treatment session.

16 Wearing appropriate new sterile gloves, hold the VARITHENA canister, twist the VARITHENA transfer unit counterclockwise and then pull up to separate from the canister (Figure 24).

17 Discard the old VARITHENA transfer unit and open a new VARITHENA transfer unit.

Make sure not to touch the sterile underside of the VARITHENA transfer unit.

18 Swab the uncovered shuttle with a fresh sterile alcohol wipe (Figure 25) and immediately place the VARITHENA transfer unit on top of the VARITHENA canister.

Gently rotate the VARITHENA transfer unit clockwise until it drops into the collar threads (Figure 26), then twist the VARITHENA transfer unit (clockwise) until it reaches a stop (Figure 27).

The VARITHENA device now ready for use for a new treatment session, following the instructions in Steps 7 to 15.

Storage and Disposal

Note: The activated VARITHENA canister should always be stored with a VARITHENA transfer unit in place in the upright position at or below 86°F (30°C) - do not refrigerate or freeze, in an appropriately controlled clean area to limit contamination.

Dispose of VARITHENA and oxygen canisters following local and state regulations for aerosol disposal.

The VARITHENA transfer unit can be disposed of as non-toxic non-clinical waste.

180 mg/18 mL Configuration: | 77.5 mg/7.75 mL Configuration:
Once the VARITHENA canister has been activated, the shelf life for the product is thirty (30) calendar days. Always write the activation date and time on the canister and verify the product has not expired prior to use. Net Contents:18 mL One canister of VARITHENA in the 180 mg/18 mL Configuration contains: 180 mg Polidocanol, 756 mg alcohol (96% v/v), 43.2 mg disodium hydrogen phosphate dihydrate, 15.3 mg potassium dihydrogen phosphate, water for injection. One canister of VARITHENA generates 90 mL of foam which, following purging instructions contained in this IFU, is sufficient to yield 45 mL of usable foam for injection. The gas mix of the foam is 65:35 O2:CO2. NDC 60635-118-01 VARITHENA 180 mg/18 mL Bi- Canister Administration Pack NDC 60635-133-01 VARITHENA 180 mg/18 mL Convenience Pack | Once the VARITHENA canister has been activated, the canister must be used within thirty (30) calendar days. Always write the activation date and time on the canister and verify the product has not expired prior to use. Net Contents:7.75 mL One canister of VARITHENA in the 77.5 mg/7.75 mL Configuration contains: 77.5 mg Polidocanol, 325.5 mg alcohol (96% v/v), 18.6 mg disodium hydrogen phosphate dihydrate, 6.6 mg potassium dihydrogen phosphate, water for injection. One canister of VARITHENA generates 30 mL of foam which, following purging instructions contained in this IFU, is sufficient to yield 15 mL of usable foam for injection. The gas mix of the foam is 65:35 O2:CO2. NDC 60635-107-01 VARITHENA 77.5 mg/7.75 mL Bi- Canister Administration Pack NDC 60635-111-01 VARITHENA 77.5 mg/7.75 mL Convenience Pack

Manufactured for Provensis Ltd by:
Biocompatibles UK Ltd
Chapman House, Weydon Lane, Farnham, Surrey, UK, GU9 8QL
Distributed by:
Biocompatibles Inc.

VARITHENA is a registered trademark of Provensis Ltd
BTG and the BTG roundel logo are registered trademarks of BTG International Ltd
Provensis Ltd, Biocompatibles UK Ltd, and Biocompatibles Inc. are BTG International group companies

PACKAGE LABEL

Principal Display Panel - Varithena Bi-Canister - NDC 60635-107-01

PACKAGE LABEL

Principal Display Panel - Varithena Pouch Label - NDC 60635-107-01

PACKAGE LABEL

Principal Display Panel - Varithena Canister Label - NDC 60635-007-01

PACKAGE LABEL

Principal Display Panel - Varithena Ancillary Pack

PACKAGE LABEL

Principal Display Panel - Varithena Convenience Box Carton - NDC 60635-111-01

PACKAGE LABEL

Principal Display Panel - Varithena Canister Label - NDC 60635-018-01

PACKAGE LABEL

Principal Display Panel - Varithena Pouch Label - NDC 60635-118-01

PACKAGE LABEL

Principal Display Panel - Varithena Bi-Canister Box - NDC 60635-118-01

PACKAGE LABEL

Principal Display Panel - Varithena Universal Administration Pack